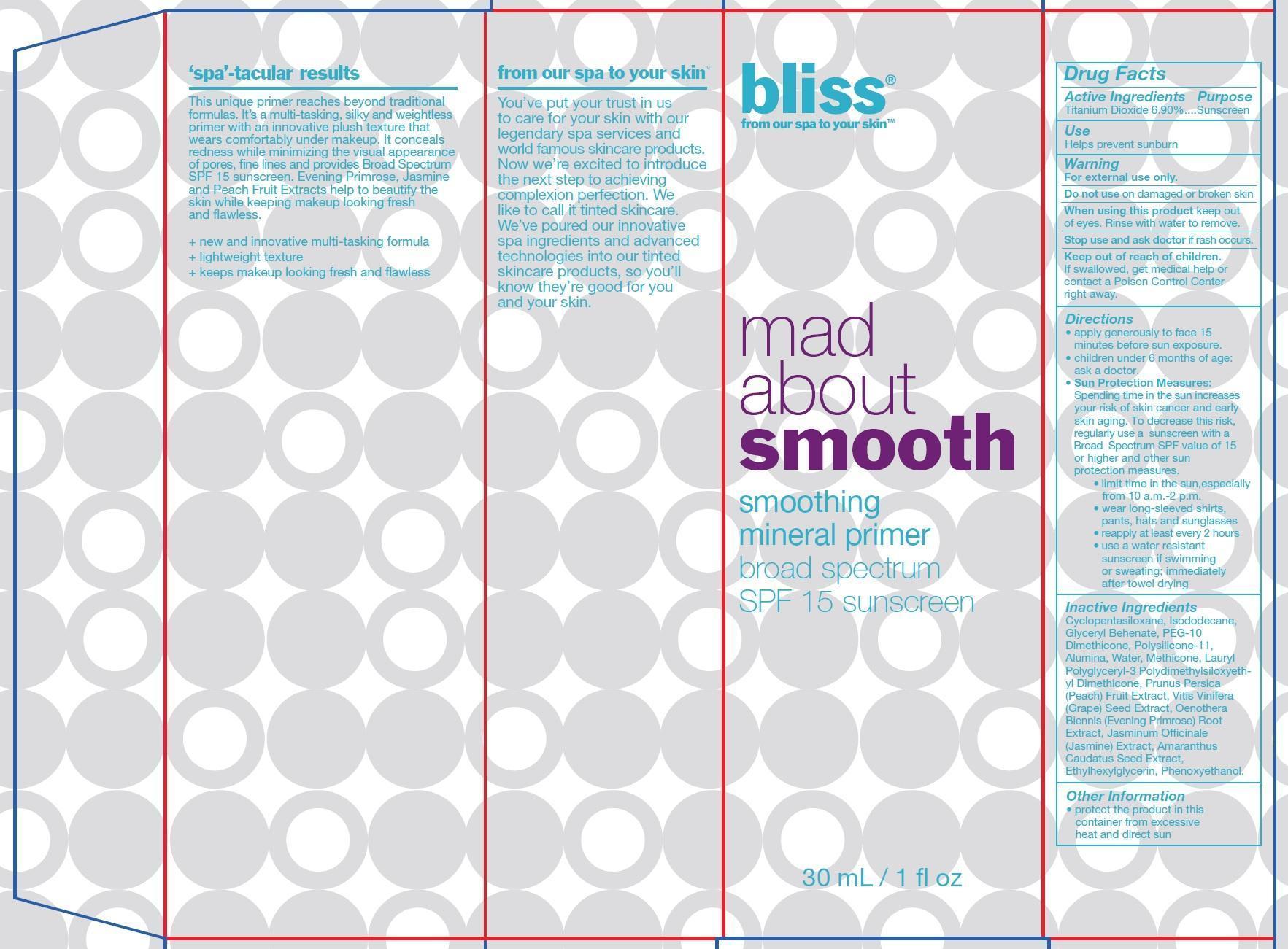 DRUG LABEL: Bliss Mad About Smooth Smoothing Mineral Primer Broad Spectrum SPF 15 Sunscreen
NDC: 69302-100 | Form: CREAM
Manufacturer: HatchBeauty Labs, LLC
Category: otc | Type: HUMAN OTC DRUG LABEL
Date: 20150723

ACTIVE INGREDIENTS: TITANIUM DIOXIDE 69 mg/1 mL
INACTIVE INGREDIENTS: CYCLOMETHICONE 5; ISODODECANE; GLYCERYL BEHENATE; DIMETHICONE/VINYL DIMETHICONE CROSSPOLYMER (SOFT PARTICLE); ALUMINUM OXIDE; WATER; PEACH; VITIS VINIFERA SEED; OENOTHERA BIENNIS ROOT; JASMINUM OFFICINALE FLOWER; AMARANTHUS CAUDATUS SEED; ETHYLHEXYLGLYCERIN; PHENOXYETHANOL

Bliss Mad About Smooth Smoothing Mineral Primer Broad Spectrum SPF 15 Sunscreen

Active Ingredients

Titanium Dioxide 6.90%

Purpose

Sunscreen

Use

Helps prevent sunburn

Warning

For external use only.

Do not use

on damaged or broken skin

When using this product

keep out of eyes. Rinse with water to remove.

Stop use and ask doctor

if rash occurs.

Keep out of reach of children.

If swallowed, get medical help or contact a Poison Control Center right away.

Directions

- apply generously to face 15 minutes before sun exposure.
- children under 6 months of age: ask a doctor.
- Sun Protection Measures: Spending time in the sun increases your risk of skin cancer and early skin aging. To decrease this risk, regularly use a sunscreen with a Broad Spectrum SPF value of 15 or higher and other sun protection measures.

• limit time in the sun,especially from 10 a.m.-2 p.m.
• wear long-sleeved shirts, pants, hats and sunglasses
• reapply at least every 2 hours
• use a water resistant sunscreen if swimming or sweating; immediately after towel drying

Inactive Ingredients

Cyclopentasiloxane, Isododecane, Glyceryl Behenate, Peg-10 Dimethicone, Polysilicone-11, Alumina, Water, Methicone, Lauryl Polyglyceryl-3 Polydimethylsiloxyethyl Dimethicone, Prunus Persica (Peach) Fruit Extract, Vitis Vinifera (Grape) Seed Extract, Oenothera Biennis (Evening Primrose) Root Extract, Jasminum Officinale (Jasmine) Extract, Amaranthus Caudatus Seed Extract, Ethylhexylglycerin, Phenoxyethanol.

Other Information

protect the product in this container from excessive heat and direct sun